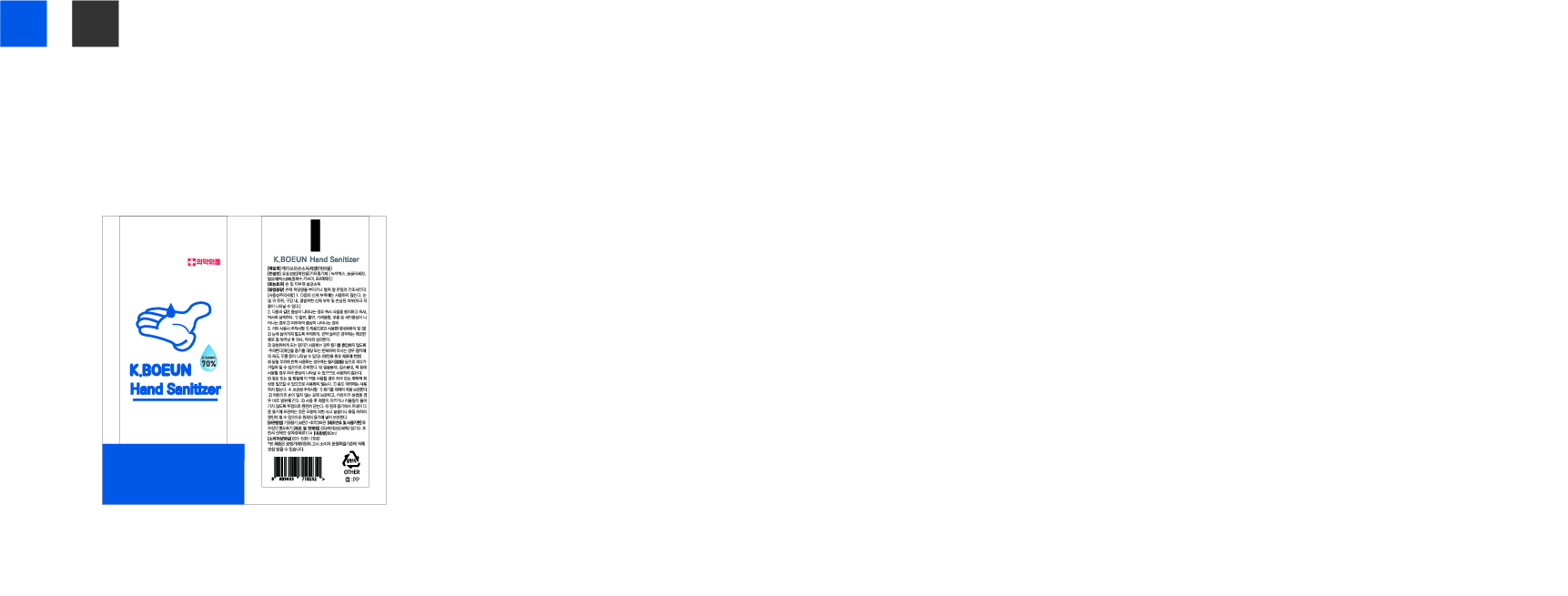 DRUG LABEL: K.Boeun Hand Sanitizer
NDC: 74724-0001 | Form: GEL
Manufacturer: K.Boeun Pharmaceutical Co.,Ltd.
Category: otc | Type: HUMAN OTC DRUG LABEL
Date: 20250609

ACTIVE INGREDIENTS: ALCOHOL 70 g/100 mL
INACTIVE INGREDIENTS: GLYCERIN; WATER

Drug Facts

ACTIVE INGREDIENT

Alcohol

INACTIVE INGREDIENT

Water, Carbomer, Triethanolamine, etc.

PURPOSE

Antiseptic

KEEP OUT OF REACH OF THE CHILDREN

INDICATIONS AND USAGE

Store under 30°C (86°F)

WARNINGS

For external use only.

Flammable, keep away from fire or flame.

When using this product keep out of eyes. If contact with eyes occurs, rinse promptly and thoroughly with water.

Stop use and ask a doctor if significant irritation or sensitization develops.

Keep out of reach of children. If swallowed, get medical help or contact a Poison Control Center right away.

DOSAGE AND ADMINISTRATION

Apply proper amount to the palm or hands.